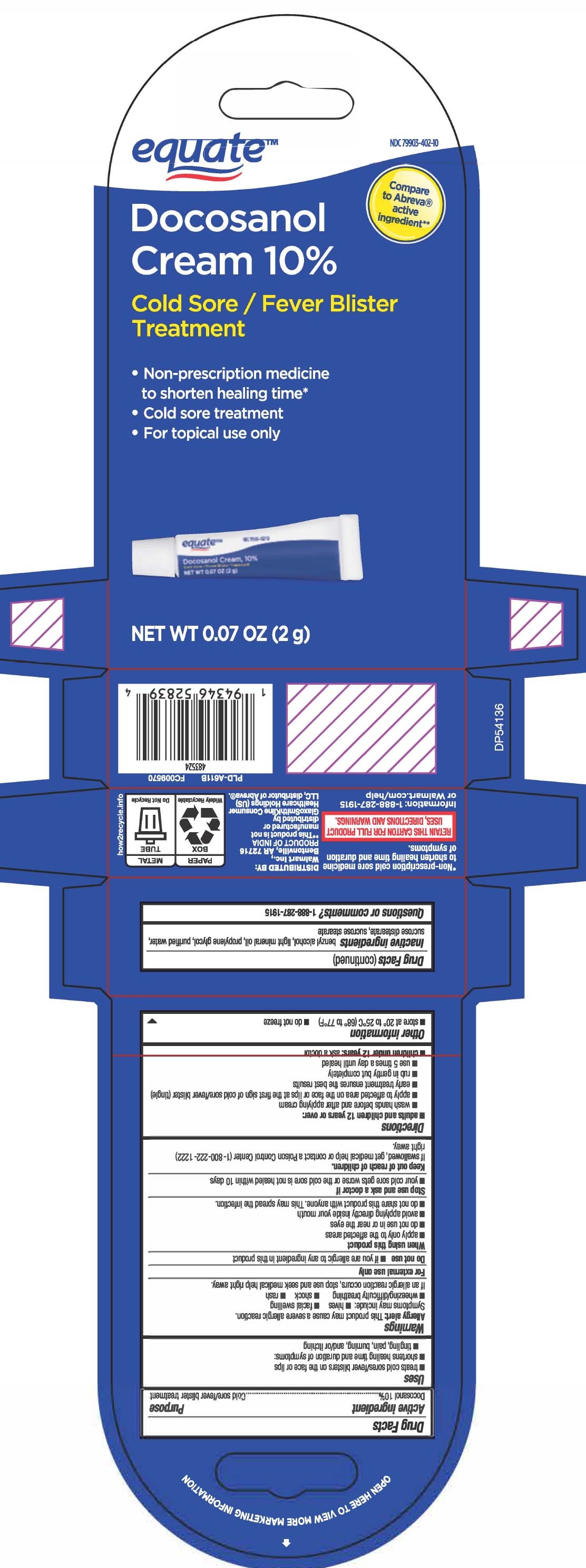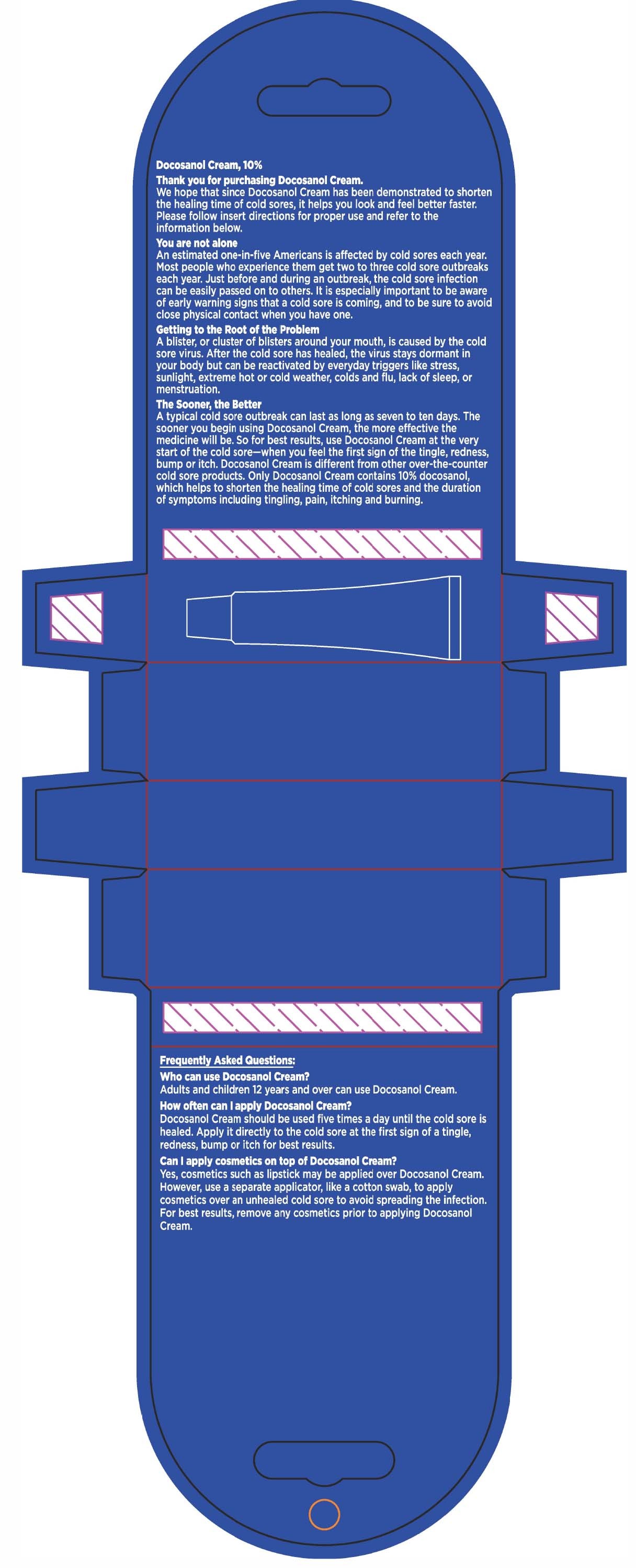 DRUG LABEL: Docosanol
NDC: 79903-402 | Form: CREAM
Manufacturer: WALMART INC. (see also Equate)
Category: otc | Type: HUMAN OTC DRUG LABEL
Date: 20260218

ACTIVE INGREDIENTS: DOCOSANOL 100 mg/1 g
INACTIVE INGREDIENTS: BENZYL ALCOHOL; LIGHT MINERAL OIL; PROPYLENE GLYCOL; WATER; SUCROSE DISTEARATE (HLB 5); SUCROSE STEARATE

Docosanol Cream, 10%

Active ingredient

Docosanol 10%

Purpose

Cold sore/fever blister treatment

Uses

- treats cold sores/fever blisters on the face or lips
- shortens healing time and duration of symptoms:
- tingling, pain, burning, and/or itching

Warnings

Allergy Alert: This product may cause a severe allergic reaction. Symptoms may include:

- hives
- facial swelling
- wheezing/difficulty breathing
- shock
- rash

If an allergic reaction occurs, stop use and seek medical help right away.

For external use only

Do not use

- if you are allergic to any ingredient in this product

When using this product

- apply only to the affected areas
- do not use in or near the eyes
- avoid applying directly inside your mouth
- do not share this product with anyone. This may spread the infection.

Stop use and ask a doctor if

- your cold sore gets worse or the cold sore is not healed within 10 days

Keep out of reach of children.

If swallowed, get medical help or contact a Poison Control Center (1-800-222-1222) right away.

Directions

- adults and children 12 years or over:
  - wash hands before and after applying cream
  - apply to affected area on the face or lips at the first sign of cold sore/fever blister (tingle).
  - early treatment ensures the best results
  - rub in gently but completely
  - use 5 times a day until healed
- children under 12 years: ask a doctor

Other information

- store at 20° to 25°C (68° to 77°F)
- do not freeze

Inactive ingredients

benzyl alcohol, light mineral oil, propylene glycol, purified water, sucrose distearate, sucrose stearate

Questions or comments?

Call 1-888-287-1915

Principal Display Panel

Compare to Abreva® active ingredient**

Docosanol

Cream 10%

Cold Sore / Fever Blister Treatment

- Non-prescription medicine to shorten healing time*
- Cold sore treatment
- for topical use only

NET WT

**This product is not manufactured or distributed by GlaxoSmithKline Consumer Healthcare Holdings (US) LLC, distributor of Abreva®.

* Non-prescription cold sore medicine to shorten healing time and duration of symptoms.

RETAIN THIS CARTON FOR FULL PRODUCT USES, DIRECTIONS AND WARNINGS

DISTRIBUTED BY:

Package Label

Equate Cold Sore/Fever Blister Treatment
Equate Cold Sore/Fever Blister Treatment Marketing Copy